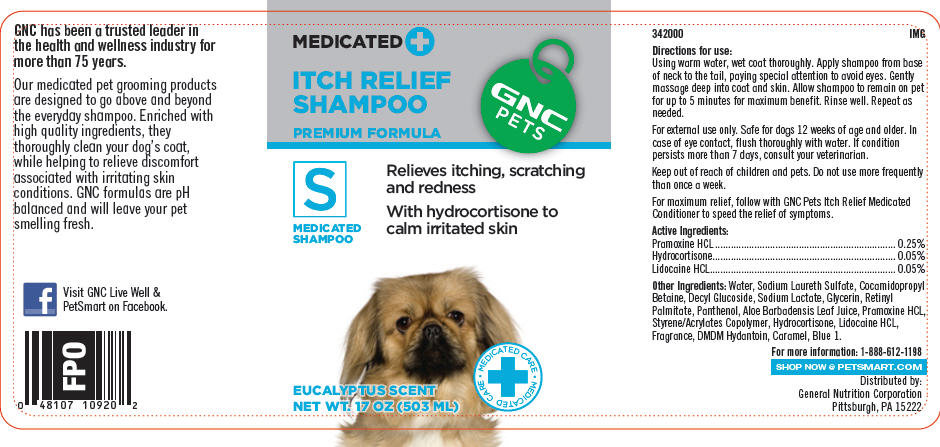 DRUG LABEL: GNC Pets Itch Relief (Premium Formula)
NDC: 43655-000 | Form: SHAMPOO
Manufacturer: General Nutrition Corporation
Category: animal | Type: OTC ANIMAL DRUG LABEL
Date: 20181105

ACTIVE INGREDIENTS: Pramoxine Hydrochloride 2.5 mg/1 mL; Hydrocortisone 0.5 mg/1 mL; Lidocaine Hydrochloride 0.5 mg/1 mL
INACTIVE INGREDIENTS: Water; Sodium Laureth-3 Sulfate; Cocamidopropyl Betaine; Decyl Glucoside; Sodium Lactate; Glycerin; Vitamin A Palmitate; Panthenol; Aloe Vera Leaf; DMDM Hydantoin; Caramel; Fd&C Blue No. 1

GNC Pets Itch Relief Shampoo (Premium Formula)

342000
IMG

INDICATIONS AND USAGE

Directions for use:

Using warm water, wet coat thoroughly. Apply shampoo from base of neck to the tail, paying special attention to avoid eyes. Gently massage deep into coat and skin. Allow shampoo to remain on pet for up to 5 minutes for maximum benefit. Rinse well. Repeat as needed.

For external use only. Safe for dogs 12 weeks of age and older. In case of eye contact, flush thoroughly with water. If condition persists more than 7 days, consult your veterinarian.

Keep out of reach of children and pets. Do not use more frequently than once a week.

For maximum relief, follow with GNC Pets Itch Relief Medicated Conditioner to speed the relief of symptoms.

Active Ingredients:
Pramoxine HCL | 0.25%
Hydrocortisone | 0.05%
Lidocaine HCL | 0.05%

Other Ingredients: Water, Sodium Laureth Sulfate, Cocamidopropyl Betaine, Decyl Glucoside, Sodium Lactate, Glycerin, Retinyl Palmitate, Panthenol, Aloe Barbadensis Leaf Juice, Pramoxine HCL, Styrene/Acrylates Copolymer, Hydrocortisone, Lidocaine HCL, Fragrance, DMDM Hydantoin, Caramel, Blue 1.

For more information: 1-888-612-1198

SHOP NOW @ PETSMART.COM

Distributed by:
General Nutrition Corporation
Pittsburgh, PA 15222

PRINCIPAL DISPLAY PANEL - 503 ML Bottle Label

MEDICATED+
ITCH RELIEF
SHAMPOO

PREMIUM FORMULA

GNC
PETS

S
MEDICATED
SHAMPOO

Relieves itching, scratching
and redness

With hydrocortisone to
calm irritated skin

• MEDICATED CARE
+
• MEDICATED CARE

EUCALYPTUS SCENT
NET WT. 17 OZ (503 ML)